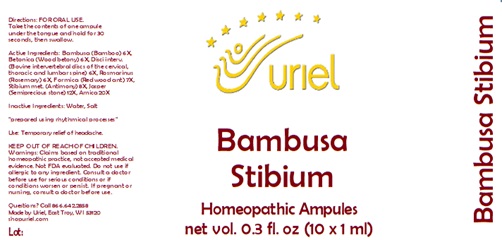 DRUG LABEL: Bambusa Stibium
NDC: 48951-2020 | Form: LIQUID
Manufacturer: Uriel Pharmacy Inc.
Category: homeopathic | Type: HUMAN OTC DRUG LABEL
Date: 20240219

ACTIVE INGREDIENTS: BAMBUSA VULGARIS WHOLE 6 [hp_X]/1 mL; STACHYS OFFICINALIS 6 [hp_X]/1 mL; BOS TAURUS INTERVERTEBRAL DISC 6 [hp_X]/1 mL; ROSMARINUS OFFICINALIS FLOWERING TOP 6 [hp_X]/1 mL; FORMICA RUFA 7 [hp_X]/1 mL; ANTIMONY 8 [hp_X]/1 mL; SILICON DIOXIDE 12 [hp_X]/1 mL; ARNICA MONTANA 20 [hp_X]/1 mL
INACTIVE INGREDIENTS: WATER; SODIUM CHLORIDE

Bambusa Stibium

INDICATIONS AND USAGE

Directions: FOR ORAL USE.

DOSAGE AND ADMINISTRATION

Take the contents of one ampule under the tongue and hold for 30 seconds, then swallow.

ACTIVE INGREDIENT

Active Ingredients: Bambusa (Bamboo) 6X, Betonica (Wood betony) 6X, Disci interv. (Bovine intervertebral discs of the cervical, thoracic and lumbar spine) 6X, Rosmarinus (Rosemary) 6X, Formica (Red wood ant) 7X, Stibium met. (Antimony) 8X, Jasper (Semiprecious stone) 12X, Arnica 20X

Inactive Ingredients: Water, Salt

"prepared using rhythmical processes"

PURPOSE

Use: Temporary relief of headache.

KEEP OUT OF REACH OF CHILDREN.

WARNINGS

Warnings: Claims based on traditional homeopathic practice, not accepted medical evidence. Not FDA evaluated. Do not use if allergic to any ingredient. Consult a doctor before use for serious conditions or if conditions worsen or persist. If pregnant or nursing, consult a doctor before use.

QUESTIONS

Questions? Call 866.642.2858 Made by Uriel, East Troy, WI 53120 shopuriel.com Lot: